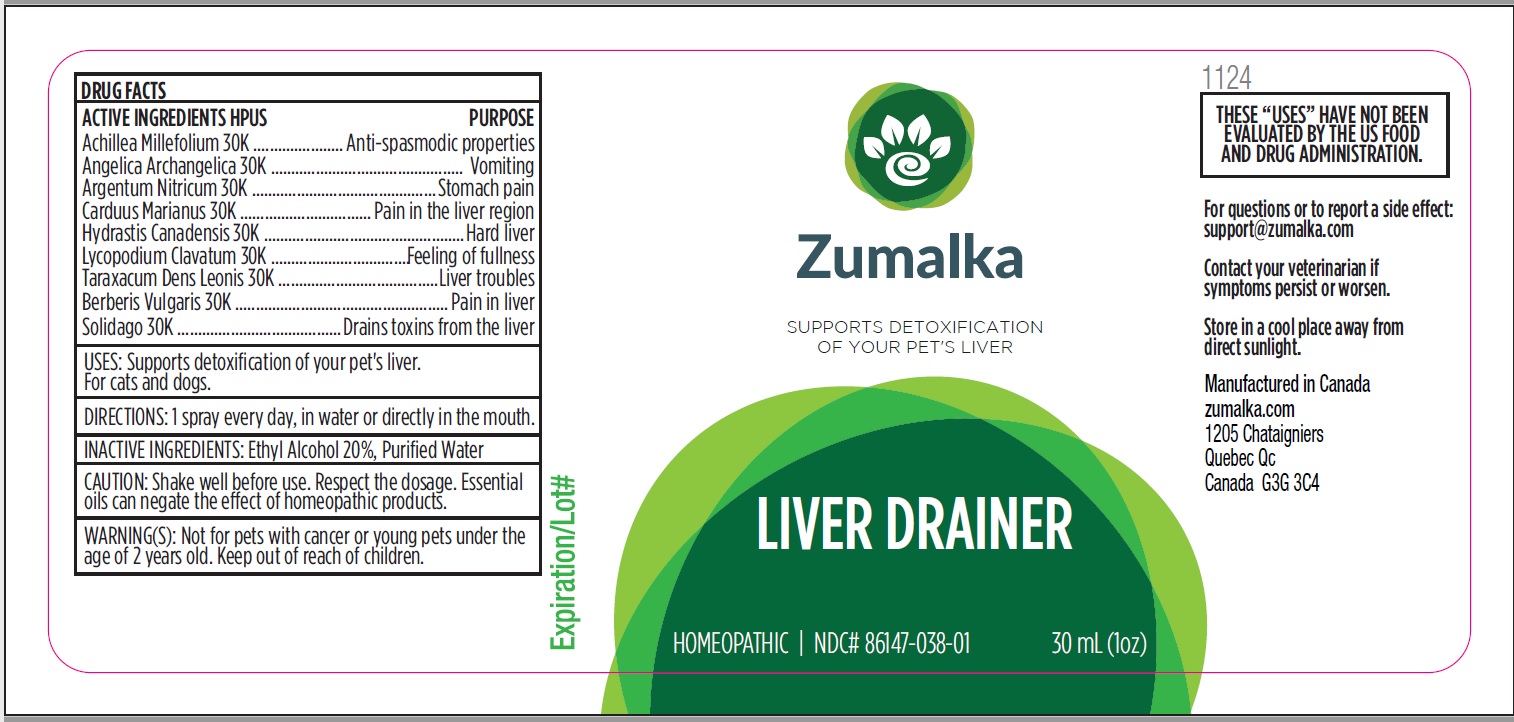 DRUG LABEL: LIVER DRAINER
NDC: 86147-038 | Form: LIQUID
Manufacturer: Groupe Cyrenne Inc.
Category: homeopathic | Type: OTC ANIMAL DRUG LABEL
Date: 20251120

ACTIVE INGREDIENTS: ACHILLEA MILLEFOLIUM WHOLE 30 [kp_C]/30 mL; ANGELICA ARCHANGELICA ROOT 30 [kp_C]/30 mL; MILK THISTLE 30 [kp_C]/30 mL; SILVER NITRATE 30 [kp_C]/30 mL; GOLDENSEAL 30 [kp_C]/30 mL; LYCOPODIUM CLAVATUM SPORE 30 [kp_C]/30 mL; TARAXACUM OFFICINALE 30 [kp_C]/30 mL; BERBERIS VULGARIS ROOT BARK 30 [kp_C]/30 mL; SOLIDAGO VIRGAUREA FLOWERING TOP 30 [kp_C]/30 mL
INACTIVE INGREDIENTS: ALCOHOL; WATER

Active ingredients Purpose

Achillea Millefolium 30k Anti-spasmodic properties

Angelica Archangelica 30k Vomiting

Carduus Marianus 30k Pain in the liver region

Argentum Nitricum 30k Stomach pain

Hydrastis Canadensis 30k Hard liver

Lycopodium Clavatum 30k Feeling of fullness

Taraxacum Dens Leonis 30k Liver troubles

Berberis Vulgaris 30k Pain in liver

Solidago 30k Drains toxins from the liver

Uses

Supports detoxification of your pet's liver. For cats and dogs.

Warnings

Keep out of reach of children. Not for pets with cancer or young pets under the age of 2 years old.

Direction

1 spray every day, in water or directly in the mouth. Stop when symptoms disappear. Not for prevention.

Inactive ingredients

Ethyl alcohol 20%, purified water

Cautions

Shake well before use. Respect the dosage. Essential oils can negate the effects of homeopathic products. Store in a cool place away from direct sunlight.